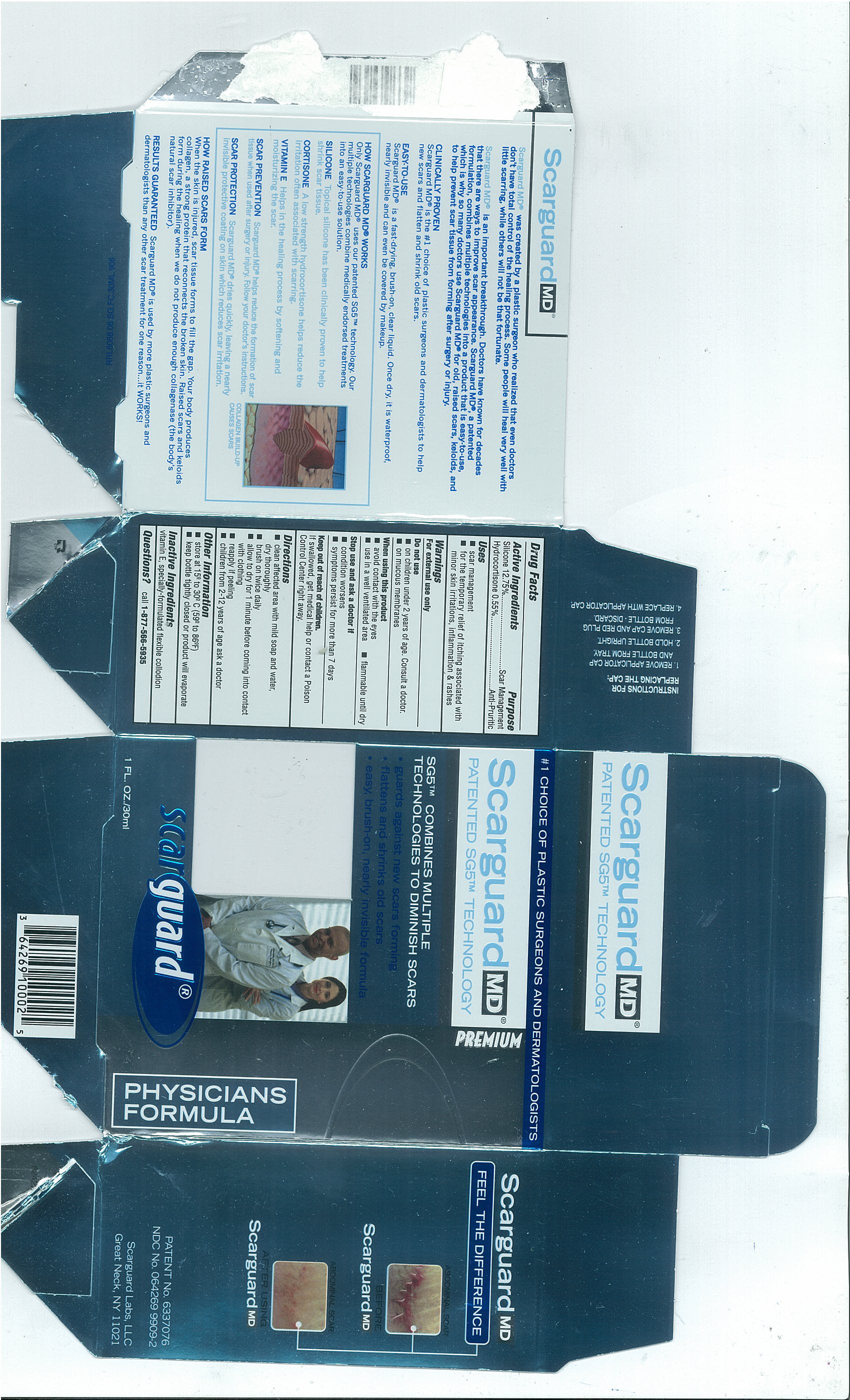 DRUG LABEL: Scarguard MD Physicians Formula
NDC: 64269-9909 | Form: LIQUID
Manufacturer: Scarguard Labs, LLC
Category: otc | Type: HUMAN OTC DRUG LABEL
Date: 20100610

ACTIVE INGREDIENTS: HYDROCORTISONE 5.5 mg/1 mL; PHENYL TRIMETHICONE 12.75 mL/100 mL
INACTIVE INGREDIENTS: ALPHA-TOCOPHEROL; PYROXYLIN; ETHER; ALCOHOL; CAMPHOR (SYNTHETIC); CASTOR OIL

Drug Facts

Active Ingredients

Silicone 12.75%
Hydrocortisone 0.55%

Purpose

Scar Management

Anti-Pruritic

Uses

- scar management
- for the temporary relief of itching associated with minor skin irritations, inflammation and rashes

Warnings

For external use only

Do not use

- on children under 2 years of age. Consult a doctor.
- on mucous membranes

When using this product

- avoid contact with the eyes
- use in a well ventilated area
- flammable until dry

Stop use and ask a doctor if

- condition worsens
- symptoms persist for more than 7 days

Keep out of reach of children

If swallowed, get medical help or contact a Poison Control Center right away.

Directions

- clean affected area with mild soap and water, dry thoroughly
- brush on twice daily
- allow to dry for 1 minute before coming into contact with clothing
- reapply if peeling
- children from 2-12 years of age ask a doctor

Other Information

- store at 15º to 30º C (59º to 86ºF)
- Keep bottle tightly closed or product will evaporate

Inactive Ingredients

vitamin E, specially-formulated flexible collodion

Questions?

call 1-877-566-5935